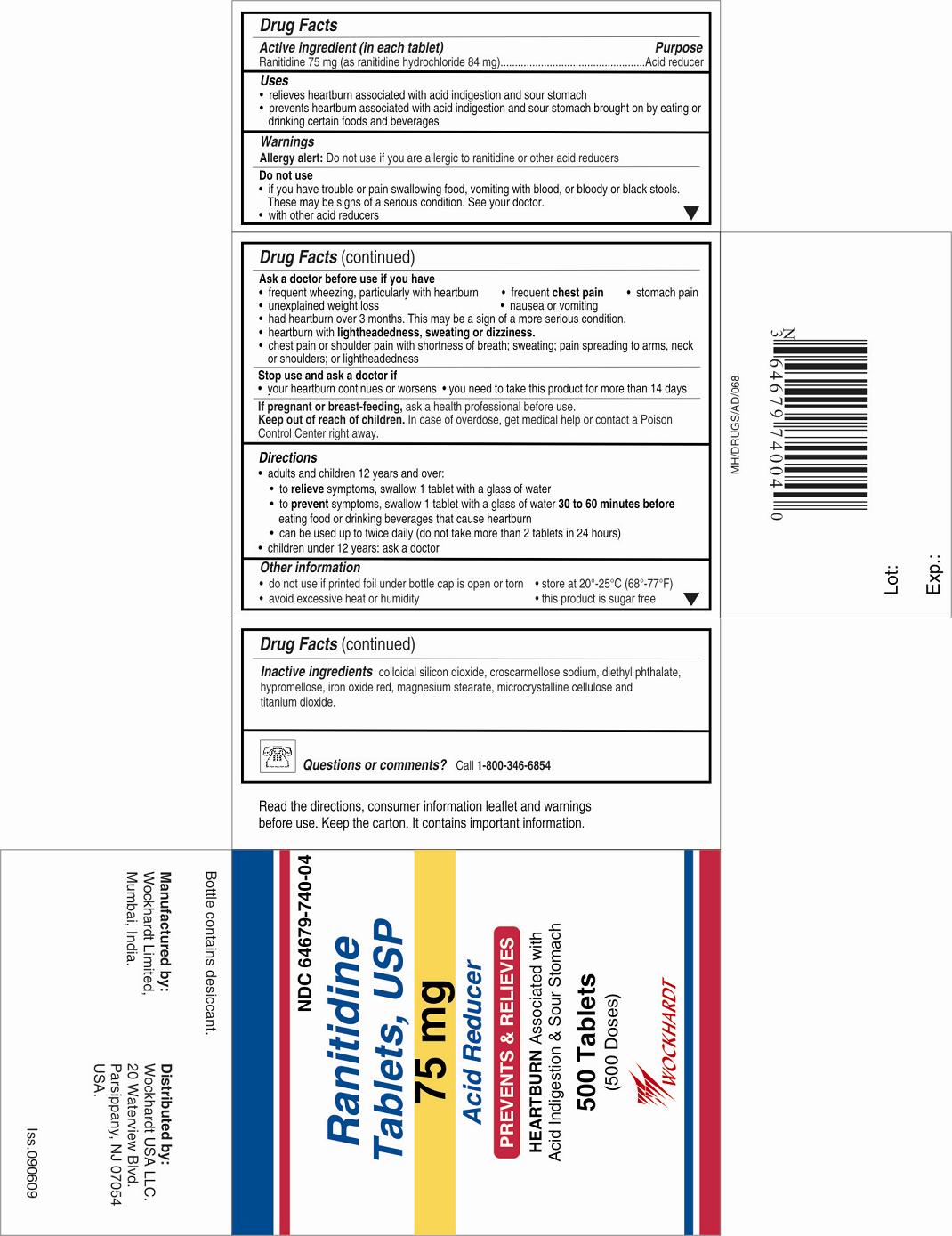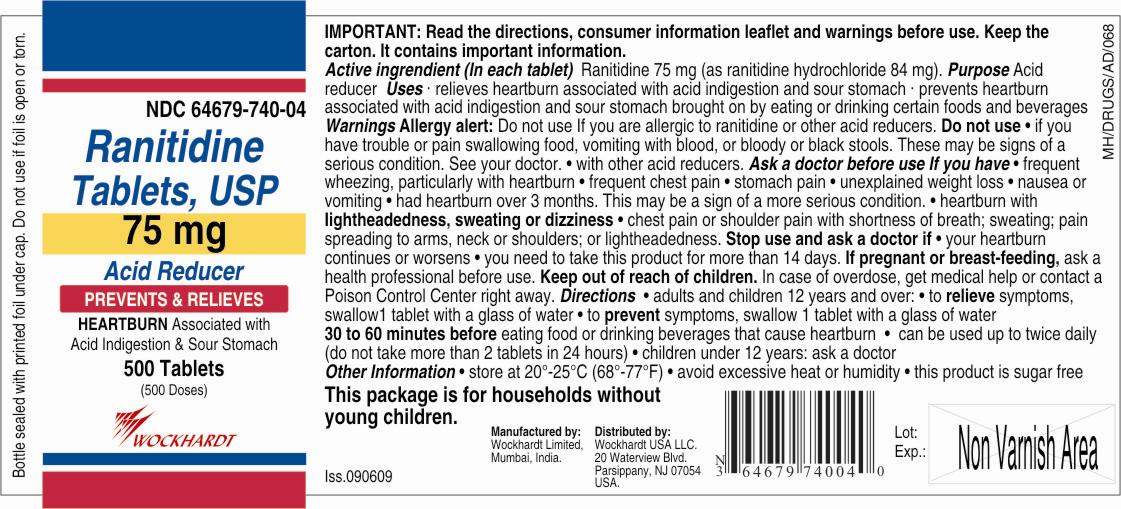 DRUG LABEL: RANITIDINE
NDC: 55648-740 | Form: TABLET, COATED
Manufacturer: WOCKHARDT LIMITED
Category: otc | Type: HUMAN OTC DRUG LABEL
Date: 20111121

ACTIVE INGREDIENTS: RANITIDINE HYDROCHLORIDE 75 mg/1 1
INACTIVE INGREDIENTS: CELLULOSE, MICROCRYSTALLINE; CROSCARMELLOSE SODIUM; MAGNESIUM STEARATE; COLLOIDAL SILICON DIOXIDE; FERRIC OXIDE RED; TITANIUM DIOXIDE; DIETHYL PHTHALATE; HYPROMELLOSES

Active ingredient (in each tablet)

Ranitidine 75 mg (as ranitidine hydrochloride 84 mg)

Purpose

Acid reducer

Uses

- relieves heartburn associated with acid indigestion and sour stomach
- prevents heartburn associated with acid indigestion and sour stomach brought on by eating or drinking certain foods and beverages

Warnings

Allergy alert: Do not use if you are allergic to ranitidine or other acid reducers

Do not use

- if you have trouble or pain swallowing food, vomiting with blood, or bloody or black stools. These may be signs of a serious condition. See your doctor.
- with other acid reducers

Ask a doctor before use if you have

- frequent wheezing, particularly with heartburn
- frequent chest pain
- stomach pain
- unexplained weight loss
- nausea or vomiting
- had heartburn over 3 months. This may be a sign of a more serious condition.
- heartburn with lightheadedness, sweating or dizziness.
- chest pain or shoulder pain with shortness of breath; sweating; pain spreading to arms, neck or shoulders; or lightheadedness

Stop use and ask a doctor if

- your heartburn continues or worsens
- you need to take this product for more than 14 days

PREGNANCY OR BREAST FEEDING

If pregnant or breast-feeding, ask a health professional before use.

Keep out of reach of children. In case of overdose, get medical help or contact a Poison Control Center right away.

Directions

- adults and children 12 years and over:
  - to relieve symptoms, swallow 1 tablet with a glass of water
  - to prevent symptoms, swallow 1 tablet with a glass of water 30 to 60 minutes before eating food or drinking beverages that cause heartburn
  - can be used up to twice daily (do not take more than 2 tablets in 24 hours)
- children under 12 years: ask a doctor

Other information

- Blister: Do not use if individual unit is open or torn
  Bottle: do not use if printed foil under bottle cap is open or torn
- store at 20°-25°C (68°-77°F)
- avoid excessive heat or humidity
- this product is sugar free

Inactive ingredients

colloidal silicon dioxide, croscarmellose sodium, diethyl phthalate, hypromellose, iron oxide red, magnesium stearate, microcrystalline cellulose and titanium dioxide.

Questions or Comments?
Call 1-800-346-6854
Read the directions, consumer information leaflet and warnings before use. Keep the carton. It contains important information.
Manufactured by:
Wockhardt Limited,
Mumbai, India.
Distributed by:
Wockhardt USA LLC.
20 Waterview Blvd.
Parsippany, NJ 07054
USA.
Iss.020410